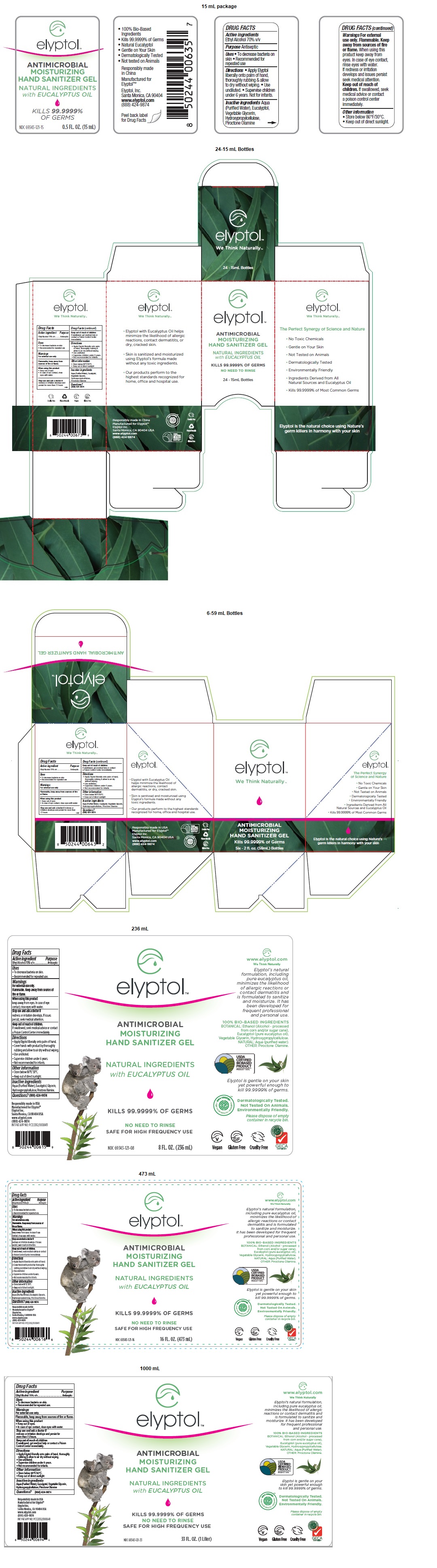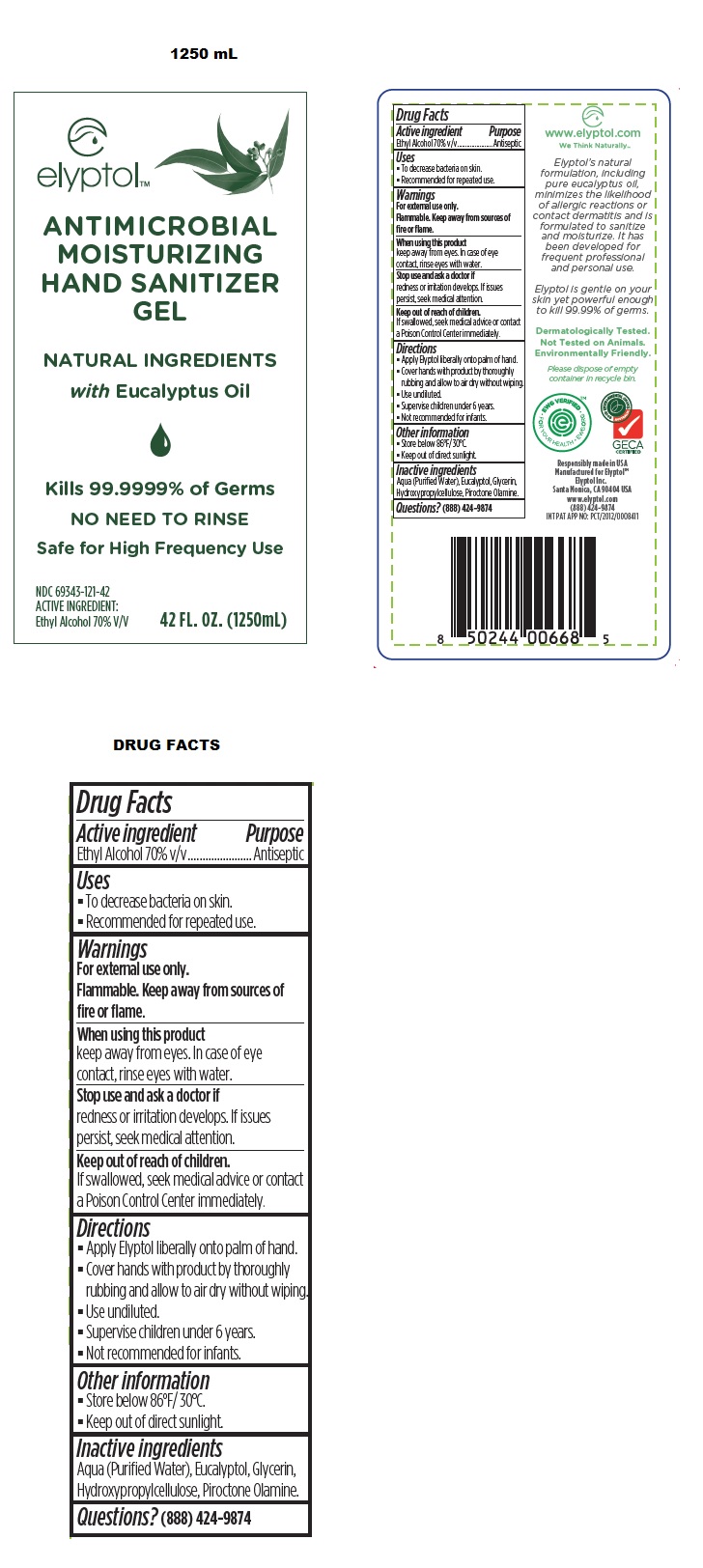 DRUG LABEL: Elyptol Antimicrobial Hand Gel
NDC: 69343-121 | Form: GEL
Manufacturer: Elyptol Inc.
Category: otc | Type: HUMAN OTC DRUG LABEL
Date: 20221219

ACTIVE INGREDIENTS: ALCOHOL 7 mL/10 mL
INACTIVE INGREDIENTS: WATER; EUCALYPTOL; GLYCERIN; HYDROXYPROPYL CELLULOSE, UNSPECIFIED; PIROCTONE OLAMINE

Elyptol Antimicrobial Hand Gel

Active ingredient

Ethyl Alcohol 70% v/v

Purpose

Antiseptic

Uses

- To decrease bacteria on skin.
- Recommended for repeated use.

Warnings

For external use only.

Flammable. Keep away from sources of fire or flame.

When using this product

keep away from eyes. In case of eye contact, rinse eyes with water.

Stop use and ask a doctor if

redness or irritation develops. If issues persist, seek medical attention.

Keep out of reach of children.

If swallowed, seek medical advice or contact a Poison Control Center immediately.

Directions

- Apply Elyptol liberally onto palm of hand.
- Cover hands with product by thoroughly rubbing and allow to air dry without wiping.
- Use undiluted.
- Supervise children under 6 years.
- Not recommended for infants.

Other Information

• Store below 86°F/30°C.
• Keep out of direct sunlight.

Inactive ingredients

Aqua (Purified Water), Eucalyptol, Glycerin, Hydroxypropylcellulose, Piroctone Olamine

Questions?

(888) 424-9874

ANTIMICROBIAL
MOISTURIZING
HAND SANITIZER GEL

NATURAL INGREDIENTS

with EUCALYPTUS OIL

KILLS 99.9999% OF GERMS

NO NEED TO RINSE

SAFE FOR HIGH FREQUENCY USE

We Think Naturally™

The Perfect Synergy of Science and Nature

• No Toxic Chemicals

• Gentle on Your Skin

• Not Tested on Animals

• Dermatologically Tested

• Environmentally Friendly

• Ingredients Derived from All Natural Sources and Eucalyptus Oil

• Kills 99.9999% of Most Common Germs

Elyptol is the natural choice using Nature’s germ killers in harmony with your skin

• Elyptol with Eucalyptus Oil helps minimize the likelihood of allergic reactions, contact dermatitis, or dry, cracked skin.

• Skin is sanitized and moisturized using Elyptol’s formula made without any toxic ingredients.

• Our products perform to the highest standards recognized for home, office and hospital use.

100% BIO-BASED INGREDIENTS
BOTANICAL: Ethanol (Alcohol - processed from corn and/or sugar cane), Eucalyptol (pure eucalyptus oil), Vegetable Glycerin, Hydroxypropylcellulose.
NATURAL: Aqua (Purified Water).
OTHER: Piroctone Olamine.

Elyptol is gentle on your skin yet powerful enough to kill 99.9999% of germs.

Dermatologically Tested.
Not Tested On Animals.
Environmentally Friendly

Please dispose of empty container in recycle bin.

Responsibly made in USA
Manufactured for Elyptol™
Elyptol Inc.
Santa Monica, CA 90404 USA
www.elyptol.com
(888) 424-9874

Cruelty Free

Please Recycle

Vegan

Gluten Free

EWG VERIFIED • EWG.ORG • FOR YOUR HEALTH